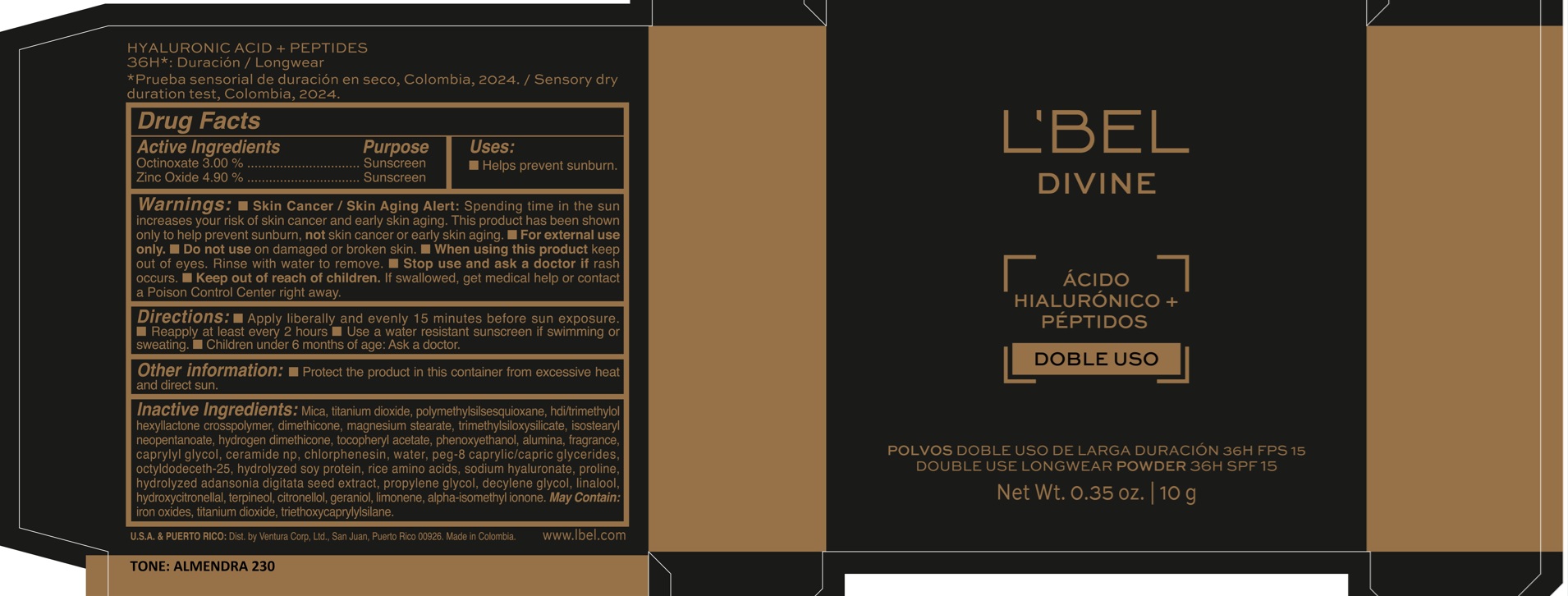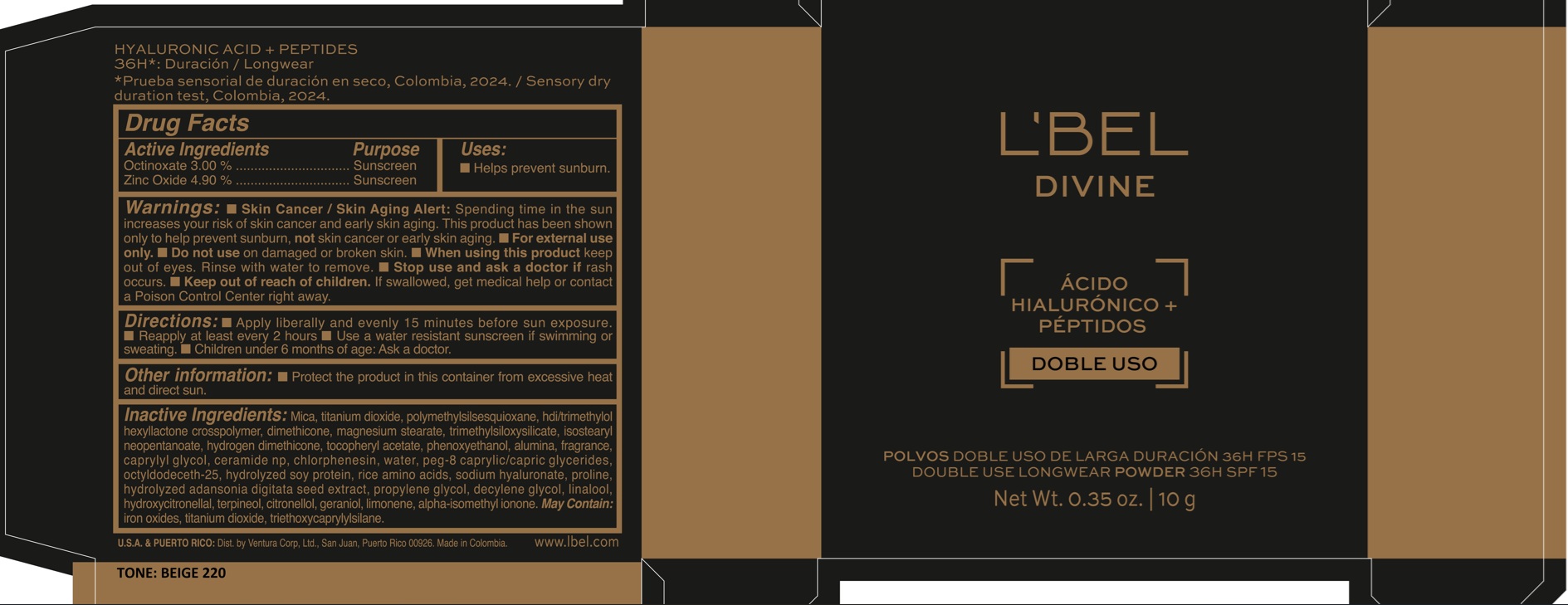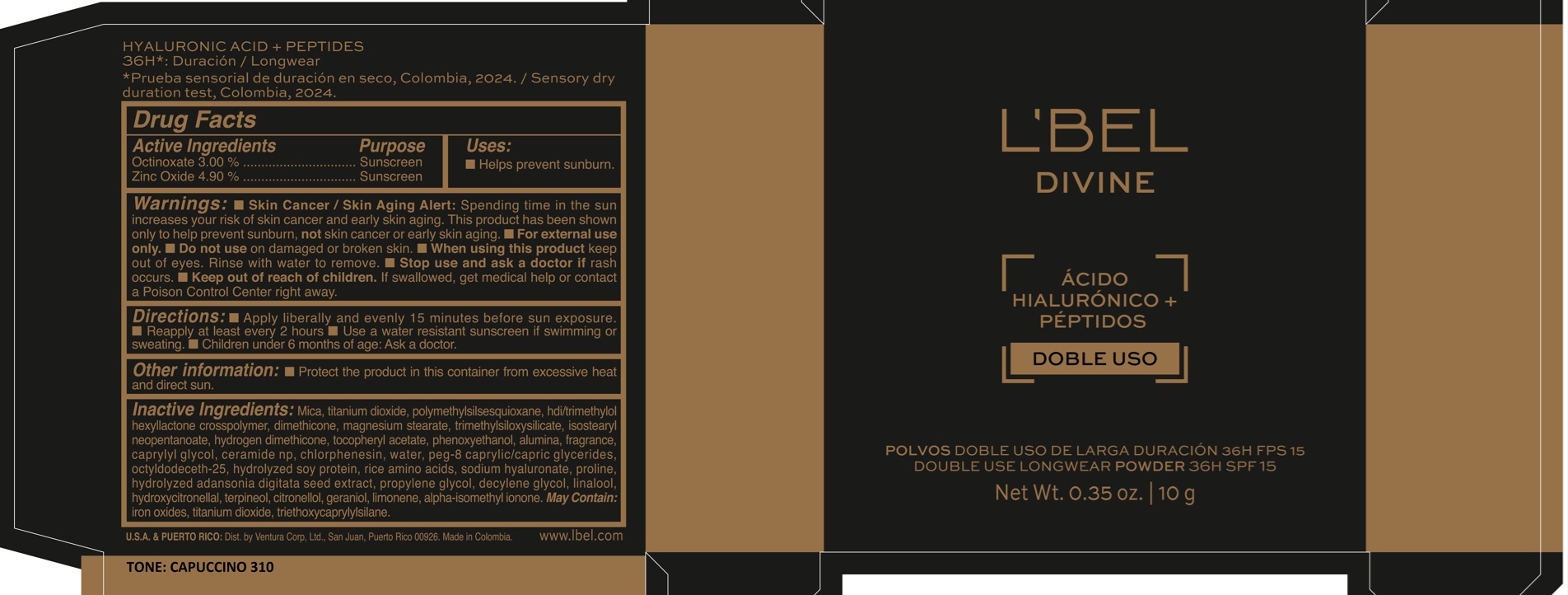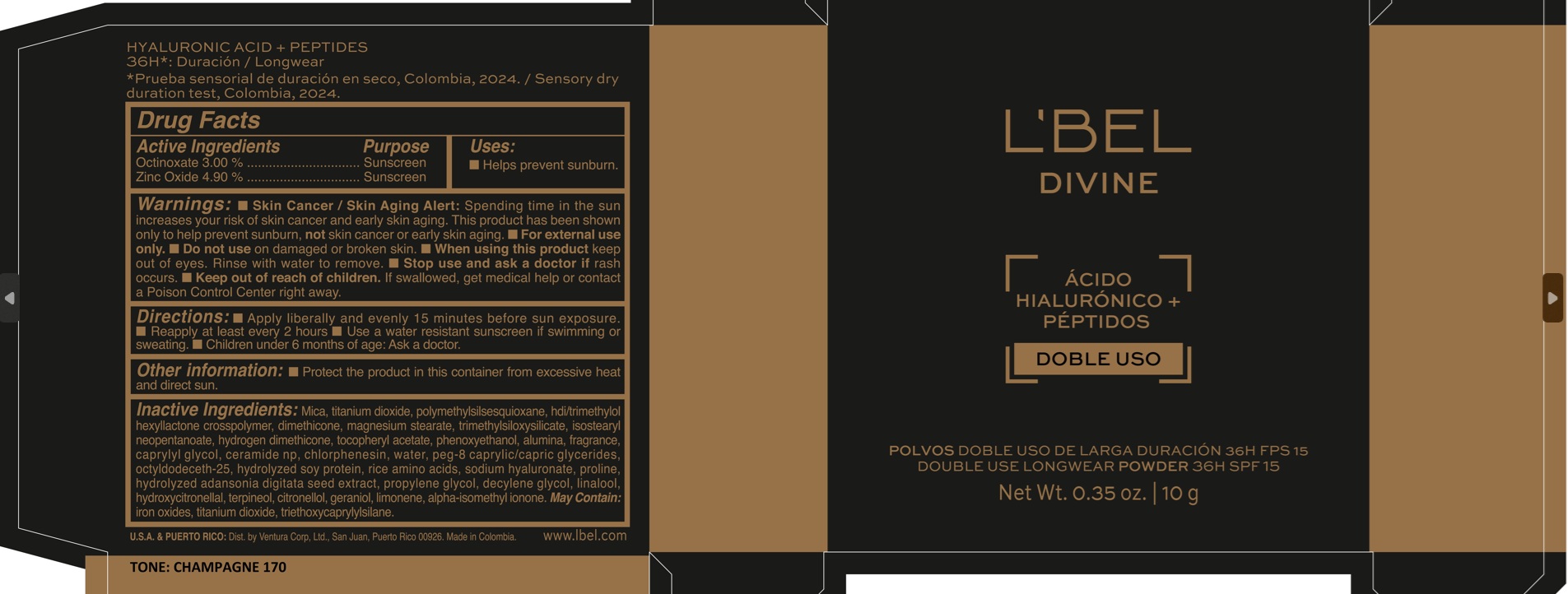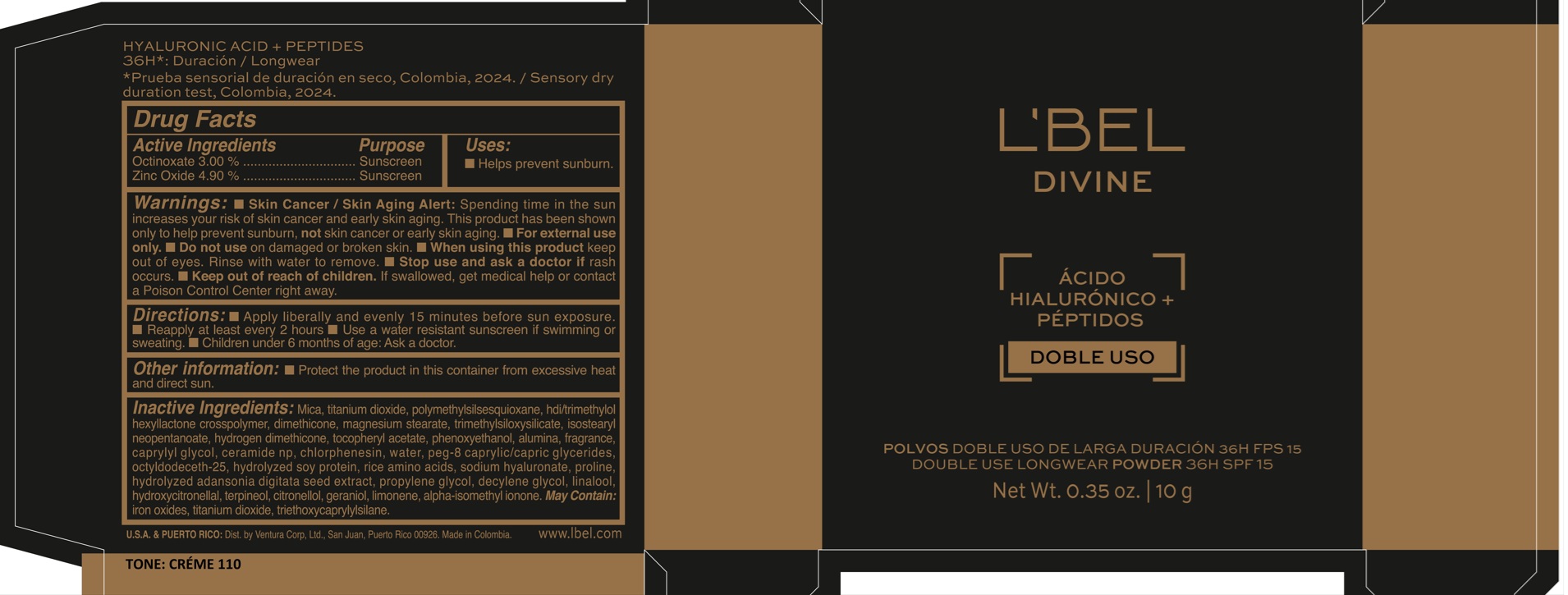 DRUG LABEL: LBEL DIVINE DOUBLE USE LONGWEAR 36H SPF 15 BEIGE 220
NDC: 14141-384 | Form: POWDER
Manufacturer: BELSTAR S.A.
Category: otc | Type: HUMAN OTC DRUG LABEL
Date: 20250304

ACTIVE INGREDIENTS: OCTINOXATE 30 mg/1 g; ZINC OXIDE 49 mg/1 g
INACTIVE INGREDIENTS: TITANIUM DIOXIDE; CAPRYLYL GLYCOL; OCTYLDODECETH-25; LIMONENE, (+/-)-; CHLORPHENESIN; HYDROXYCITRONELLAL; TERPINEOL; MICA; PHENOXYETHANOL; TRIMETHYLSILOXYSILICATE (M/Q 0.6-0.8); HYDROLYZED SOY PROTEIN (ENZYMATIC; 2000 MW); GERANIOL; POLYMETHYLSILSESQUIOXANE (4.5 MICRONS); RICE AMINO ACIDS; SODIUM HYALURONATE; PROLINE; ALPHA-TOCOPHEROL ACETATE; WATER; PEG-8 CAPRYLIC/CAPRIC GLYCERIDES; ALPHA-ISOMETHYL IONONE; IRON OXIDES; CERAMIDE NP; HYDROGEN DIMETHICONE (20 CST); CITRONELLOL; MAGNESIUM STEARATE; DECYLENE GLYCOL; PROPYLENE GLYCOL; LINALOOL; HDI/TRIMETHYLOL HEXYLLACTONE CROSSPOLYMER; ALUMINA; TRIETHOXYCAPRYLYLSILANE; DIMETHICONE; ISOSTEARYL NEOPENTANOATE

LBEL DIVINE DOUBLE USE LONGWEAR 36H SPF 15

Active Ingredients

OCTINOXATE 3.00 %

ZINC OXIDE 4.90 %

Purpose

Sunscreen

Uses

- Helps prevent sunburn.

Warnings

- Skin Cancer / Skin Aging Alert: Spending time in the sun increases your risk of skin cancer and early skin aging. This product has been shown only to help prevent sunburn, not skin cancer or early skin aging.
- For external use only.

Do not use

on damaged or broken skin.

When using this product

keep out of eyes. Rinse with water to remove.

Stop use and ask a doctor if

rash occurs.

Keep out of reach of children.

If swallowed, get medical help or contact a Poison Control Center right away.

Directions

- Apply liberally and evenly 15 minutes before sun exposure.
- Reapply at least every 2 hours
- Use a water resistant sunscreen if swimming or sweating.
- Children under 6 months of age: Ask a doctor

Other information

- Protect the product in this container from excessive heat and direct sun.

Inactive ingredients

Mica, titanium dioxide, polymethylsilsesquioxane, hdi/trimethylol hexyllactone crosspolymer, dimethicone, magnesium stearate, trimethylsiloxysilicate, isostearyl neopentanoate, hydrogen dimethicone, tocopheryl acetate, phenoxyethanol, alumina, fragrance, caprylyl glycol, ceramide np, chlorphenesin, water, peg-8 caprylic/capric glycerides, octyldodeceth-25, hydrolyzed soy protein, rice amino acids, sodium hyaluronate, proline, hydrolyzed adansonia digitata seed extract, propylene glycol, decylene glycol, linalool, hydroxycitronellal, terpineol, citronellol, geraniol, limonene, alpha-isomethyl ionone. May Contain :iron oxides, titanium dioxide, triethoxycaprylylsilane.